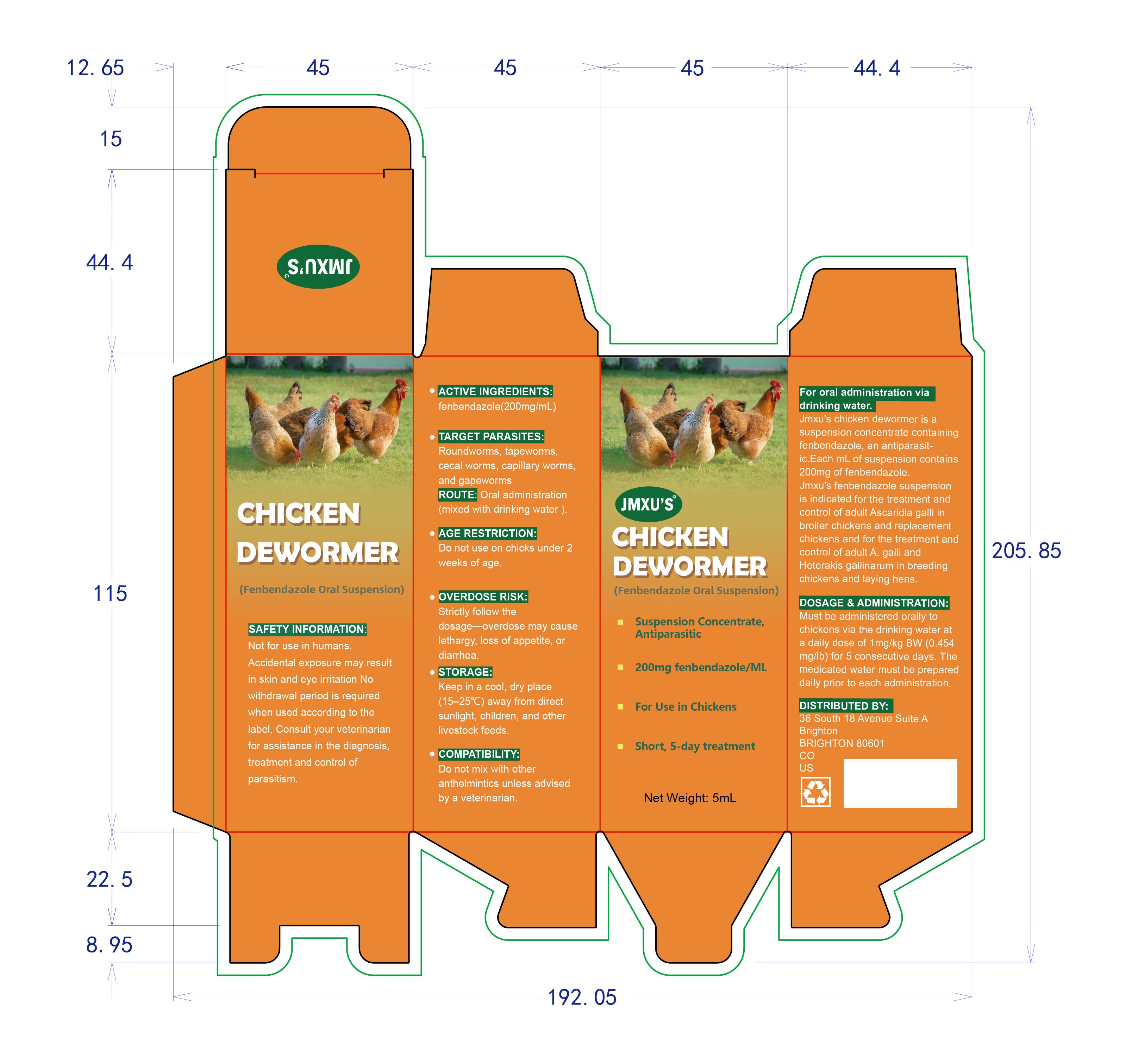 DRUG LABEL: jmxus Chicken dewormer
NDC: 86216-006 | Form: SUSPENSION
Manufacturer: Pet Professional inc.
Category: animal | Type: OTC ANIMAL DRUG LABEL
Date: 20251115

ACTIVE INGREDIENTS: FENBENDAZOLE 200 mg/1 mL

jmxus chicken dewormer

INDICATIONS & USAGE SECTION

Must be administered orally to chickens via the drinking water at a daily dose of 1mg/kg BW (0.454mg/lb) for 5 consecutive days. The medicated water must be prepared daily prior to each administration.